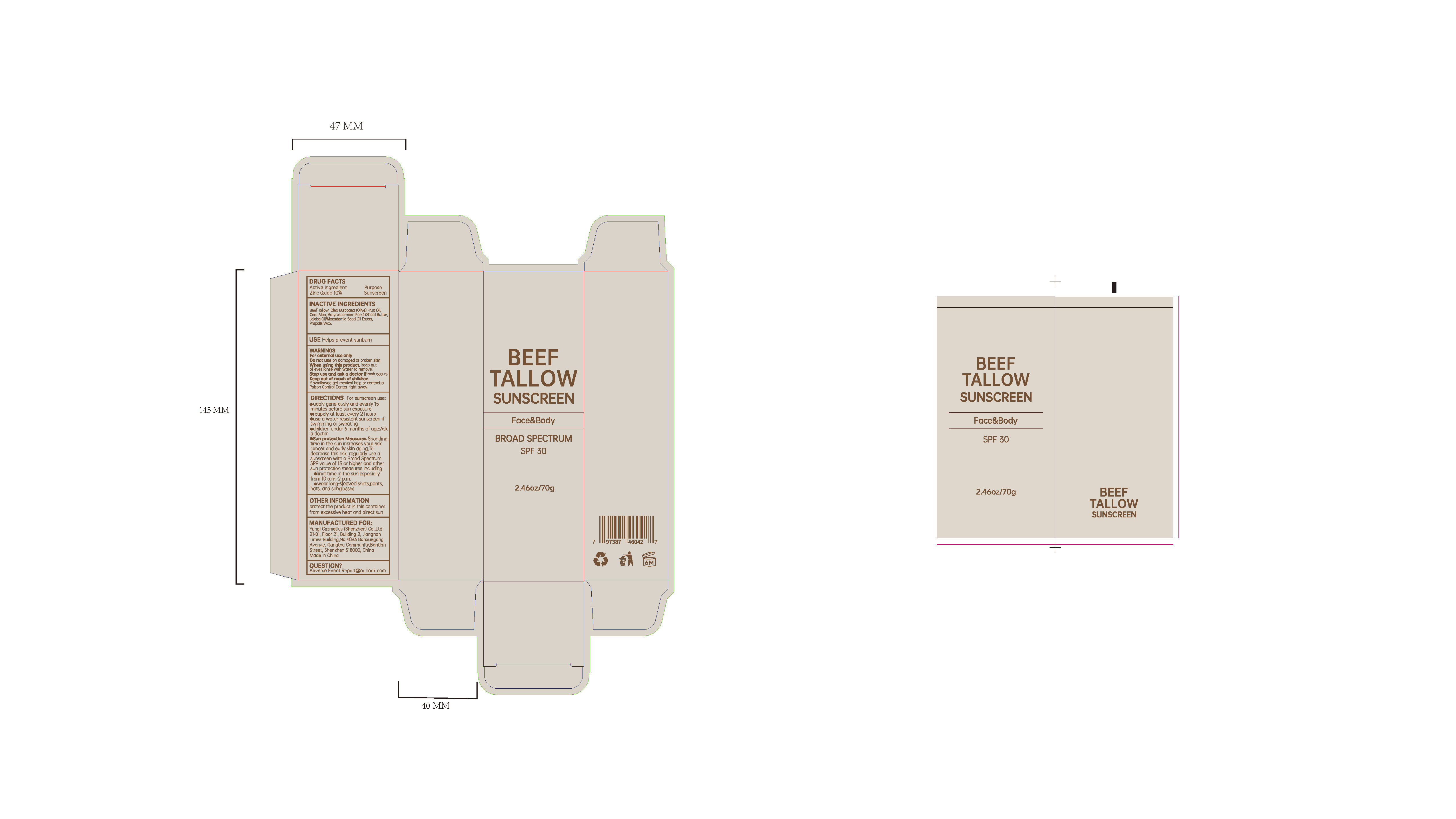 DRUG LABEL: BEEF TALLOW SUNSCREEN
NDC: 84763-003 | Form: CREAM
Manufacturer: Yunqi Cosmetics (Shenzhen) Co., Ltd
Category: otc | Type: HUMAN OTC DRUG LABEL
Date: 20250424

ACTIVE INGREDIENTS: ZINC OXIDE 0.1 g/1 g
INACTIVE INGREDIENTS: WHITE WAX; PROPOLIS WAX; JOJOBA OIL, RANDOMIZED; BUTYROSPERMUM PARKII (SHEA) BUTTER; BEEF TALLOW; OLEA EUROPAEA (OLIVE) FRUIT OIL

BEEF TALLOW SUNSCREEN

ACTIVE INGREDIENT

Zinc Oxide

PURPOSE

Sunscreen

INDICATIONS AND USAGE

USE Helps prevent sunburn

WARNINGS

For external use only

Do not use on damaged or broken skin

when using this product, keep outof eyes.Rlnse wlt water to remove.

Stop use and ask a doctor if rash occurs

KEEP OUT OF REACH OF CHILDREN

IF swallowed,get medical help or contact aPolson Control center right away.

DOSAGE AND ADMINISTRATION

DIRECTIONS For sunscreen use:
apply generously and evenly 15minutes before sun exposure
reapply at least every 2 hours
use a water resistant sunscreen if swirmmming or sweating
children under 6 months of age:Aska doctore
Sun protectlon Measures.Spendingtime in the sun increases your riskcancer and early skn aging.Todecrease this risk,regularly use asunscreen with a Broad SpectrumSPF value of 15 or higher and othersun protection measures including
limit time in the sun,especiallyfrom 10 a.m.-2 p.m.
wear long-sleeved shirts,pants,hats, and sunglasses

INACTIVE INGREDIENT

Beef Tallow
Olea Europaea (Olive)Fruit Oil
Cera Alba
Butyrospermum Parkii (Shea) Butter
Jojoba Oil/Macadamia Seed Oil Esters
Propolis Wax